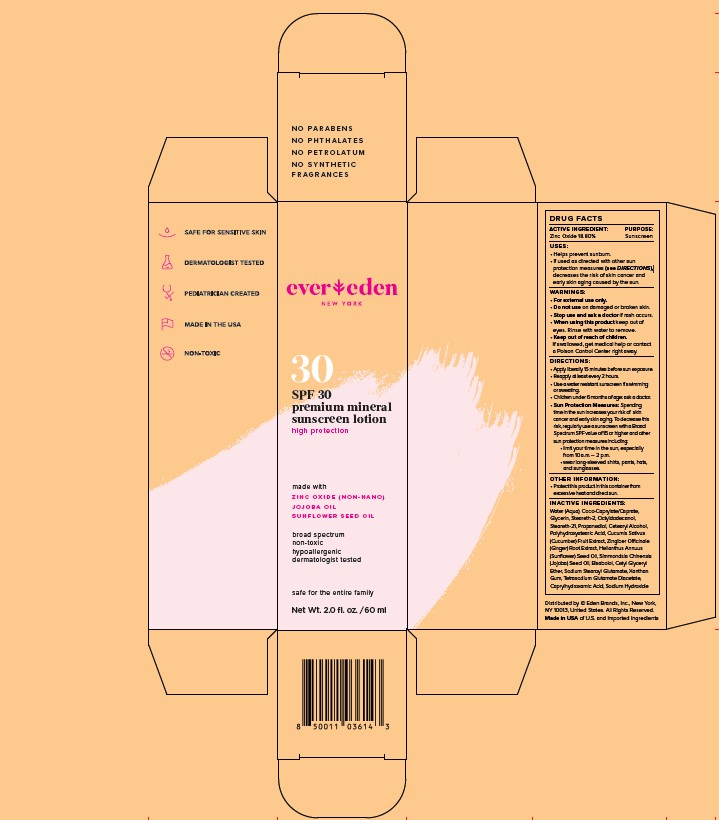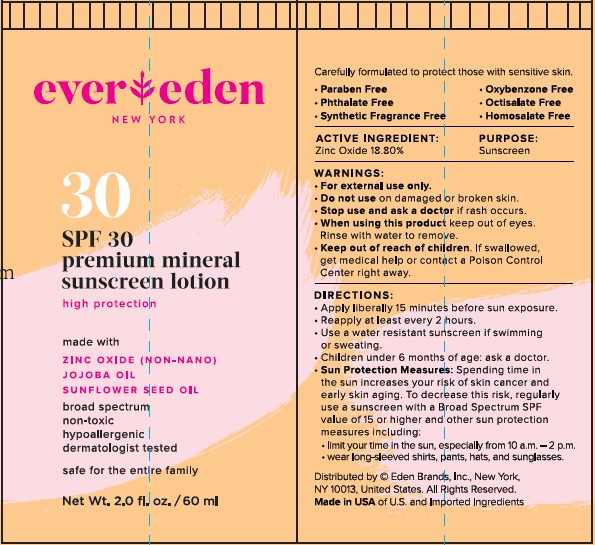 DRUG LABEL: Evereden Premium Mineral Sunscreen SPF 30
NDC: 72113-102 | Form: LOTION
Manufacturer: Eden Brands Inc
Category: otc | Type: HUMAN OTC DRUG LABEL
Date: 20241213

ACTIVE INGREDIENTS: ZINC OXIDE 188 mg/1 g
INACTIVE INGREDIENTS: OCTYLDODECANOL; POLYHYDROXYSTEARIC ACID (2300 MW); CUCUMIS SATIVUS WHOLE; ZINGIBER OFFICINALE WHOLE; XANTHAN GUM; TETRASODIUM GLUTAMATE DIACETATE; CAPRYLHYDROXAMIC ACID; WATER; COCO-CAPRYLATE/CAPRATE; STEARETH-2; STEARETH-21; PROPANEDIOL; SODIUM HYDROXIDE; GLYCERIN; HELIANTHUS ANNUUS WHOLE; SIMMONDSIA CHINENSIS SEED; CETYL GLYCERYL ETHER; SODIUM STEAROYL GLUTAMATE

SPF30 Premium Mineral Sunscreen Lotion

STATEMENT OF IDENTITY

SPF30 Premium Mineral Sunscreen Lotion

ACTIVE INGREDIENT: Zinc Oxide, 18.8%

PURPOSE: Sunscreen

USES:

- Helps prevent sunburn.
- If used as directed with other sun protection measures (see Directions), decreases the risk of skin cancer and early skin aging caused by the sun.

WARNINGS:

- For external use only.

Do not use on damaged or broken skin.

Stop use and ask a doctor if rash occurs.

When using this product keep out of eyes. Rinse with water to remove.

Keep out of reach of children. If swallowed, get medical help or contact a Poison Control Center right away.

DIRECTIONS:

- Apply liberally 15 minutes before sun exposure

- Reapply at least every 2 hours

- Use a water resistant sunscreen if swimming or sweating

- Children under 6 months of age: ask a doctor

- Sun Protection Measures: Spending time in the sun increases your risk of skin cancer and early skin aging. To decrease this risk, regularly use a sunscreen with a Broad Spectrum SPF value of 15 or higher and other sun protection measures including:

-limit your time in the sun, especially from 10am-2pm

-wear long-sleeved shirts, pants, hats, and sunglasses.

INACTIVE INGREDIENTS:

Water (Aqua), Coco-Caprylate/Caprate, Glycerin, Steareth-2, Octyldodecanol, Steareth-21, Propanediol, Cetearyl Alcohol, Polyhydroxystearic Acid, Cucumis Sativus (Cucumber) Fruit Extract, Zingiber Officinale (Ginger) Root Extract, Helianthus Annuus (Sunflower) Seed Oil, Simmondsia Chinensis (Jojoba) Seed Oil, Bisabolol, Cetyl Glyceryl Ether, Sodium Stearoyl Glutamate, Xanthan Gum, Tetrasodium Glutamate Diacetate, Caprylhydroxamic Acid, Sodium Hydroxide